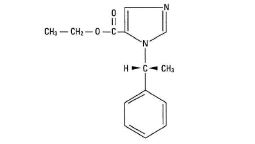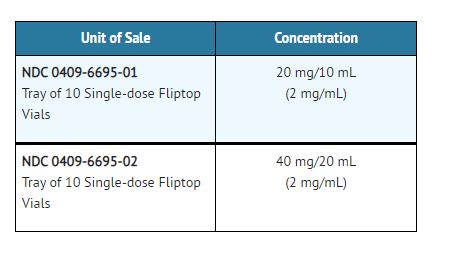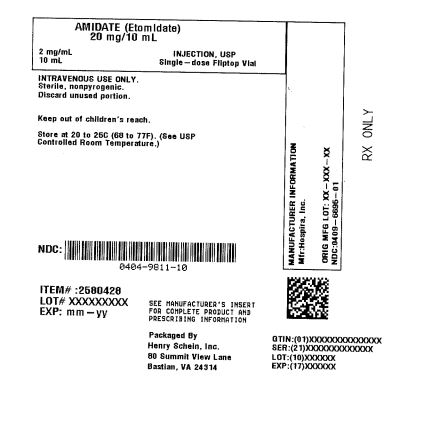 DRUG LABEL: Amidate
NDC: 0404-9811 | Form: INJECTION, SOLUTION
Manufacturer: Henry Schein, Inc.
Category: prescription | Type: HUMAN PRESCRIPTION DRUG LABEL
Date: 20251027

ACTIVE INGREDIENTS: Etomidate 2 mg/1 mL
INACTIVE INGREDIENTS: WATER

Amidate™
(etomidate) injection, USP
2 mg/mL
For intravenous use
EN-6082

DESCRIPTION

AMIDATE (Etomidate Injection, USP) is a sterile, nonpyrogenic solution. Each milliliter contains etomidate, 2 mg, propylene glycol 35% v/v. The pH is 6.0 (4.0 to 7.0).

It is intended for the induction of general anesthesia by intravenous injection.

The drug etomidate is chemically identified as (R)-(+)-ethyl-1-(1-phenylethyl)-1H-imidazole-5-carboxylate and has the following structural formula:

CLINICAL PHARMACOLOGY

Etomidate is a general anesthetic without analgesic activity. Intravenous injection of etomidate produces anesthesia characterized by a rapid onset of action, usually within one minute. Duration of anesthesia is dose dependent but relatively brief, usually three to five minutes when an average dose of 0.3 mg/kg is employed. Immediate recovery from anesthesia (as assessed by awakening time, time needed to follow simple commands and time to perform simple tests after anesthesia as well as they were performed before anesthesia), based upon data derived from short operative procedures where intravenous etomidate was used for both induction and maintenance of anesthesia, is about as rapid as, or slightly faster than, immediate recovery after similar use of thiopental. These same data revealed that the immediate recovery period will usually be shortened in adult patients by the intravenous administration of approximately 0.1 mg of intravenous fentanyl, one or two minutes before induction of anesthesia, probably because less etomidate is generally required under these circumstances (consult the package insert for fentanyl before using).

The most characteristic effect of intravenous etomidate on the respiratory system is a slight elevation in arterial carbon dioxide tension (PaCO2) (see ADVERSE REACTIONS).

Reduced cortisol plasma levels have been reported with induction doses of 0.3 mg/kg etomidate. These persist for approximately 6 to 8 hours and appear to be unresponsive to Adrenocorticotropic hormone (ACTH) administration.

The intravenous administration of up to 0.6 mg/kg of etomidate to patients with severe cardiovascular disease has little or no effect on myocardial metabolism, cardiac output, peripheral circulation or pulmonary circulation. The hemodynamic effects of etomidate have in most cases been qualitatively similar to those of thiopental sodium, except that the heart rate tended to increase by a moderate amount following administration of thiopental under conditions where there was little or no change in heart rate following administration of etomidate. However, clinical data indicates that etomidate administration in geriatric patients, particularly those with hypertension, may result in decreases in heart rate, cardiac index, and mean arterial blood pressure. There are insufficient data concerning use of etomidate in patients with recent severe trauma or hypovolemia to predict cardiovascular response under such circumstances.

Clinical experience and special studies to date suggest that standard doses of intravenous etomidate ordinarily neither elevate plasma histamine nor cause signs of histamine release.

Limited clinical experience, as well as animal studies, suggests that inadvertent intra-arterial injection of etomidate, unlike thiobarbiturates, will not usually be followed by necrosis of tissue distal to the injection site. Intra-arterial injection of etomidate is, however, not recommended.

Etomidate induction is associated with a transient 20% to 30% decrease in cerebral blood flow. This reduction in blood flow appears to be uniform in the absence of intracranial space occupying lesions. As with other intravenous induction agents, reduction in cerebral oxygen utilization is roughly proportional to the reduction in cerebral blood flow. In patients with and without intracranial space occupying lesions, etomidate induction is usually followed by a moderate lowering of intracranial pressure, lasting several minutes. All of these studies provided for avoidance of hypercapnia. Information concerning regional cerebral perfusion in patients with intracranial space occupying lesions is too limited to permit definitive conclusions.

Preliminary data suggests that etomidate will usually lower intraocular pressure moderately.

Etomidate is rapidly metabolized in the liver. Minimal anesthetic plasma levels of unchanged drug are equal to or higher than 0.23 mcg/mL; they decrease rapidly up to 30 minutes following injection and thereafter more slowly with a half-life value of about 75 minutes. Approximately 75% of the administered dose is excreted in the urine during the first day after injection. The chief metabolite is R-(+)-1-(1-phenylethyl)-1H-imidazole-5-carboxylic acid, resulting from hydrolysis of etomidate, and accounts for about 80% of the urinary excretion. Limited pharmacokinetic data in patients with cirrhosis and esophageal varices suggest that the volume of distribution and elimination half-life of etomidate are approximately double that seen in healthy subjects.

In clinical studies, elderly patients demonstrated decreased initial distribution volumes and total clearance of etomidate. Protein binding of etomidate to serum albumin was also significantly decreased in these individuals.

Reduced plasma cortisol and aldosterone levels have been reported following induction doses of etomidate. These results persist for approximately 6 to 8 hours and appear to be unresponsive to ACTH stimulation. This probably represents blockage of 11 beta-hydroxylation within the adrenal cortex.

INDICATIONS AND USAGE

AMIDATE is indicated by intravenous injection for the induction of general anesthesia. When considering use of AMIDATE, the usefulness of its hemodynamic properties (see CLINICAL PHARMACOLOGY) should be weighed against the high frequency of transient skeletal muscle movements (see ADVERSE REACTIONS).

Intravenous AMIDATE is also indicated for the supplementation of subpotent anesthetic agents, such as nitrous oxide in oxygen, during maintenance of anesthesia for short operative procedures such as dilation and curettage or cervical conization.

CONTRAINDICATIONS

AMIDATE is contraindicated in patients who have shown hypersensitivity to it.

WARNINGS

INTRAVENOUS AMIDATE SHOULD BE ADMINISTERED ONLY BY PERSONS TRAINED IN THE ADMINISTRATION OF GENERAL ANESTHETICS AND IN THE MANAGEMENT OF COMPLICATIONS ENCOUNTERED DURING THE CONDUCT OF GENERAL ANESTHESIA.

BECAUSE OF THE HAZARDS OF PROLONGED SUPPRESSION OF ENDOGENOUS CORTISOL AND ALDOSTERONE PRODUCTION, THIS FORMULATION IS NOT INTENDED FOR ADMINISTRATION BY PROLONGED INFUSION.

Pediatric Neurotoxicity: Published animal studies demonstrate that the administration of anesthetic and sedation drugs that block NMDA receptors and/or potentiate GABA activity increase neuronal apoptosis in the developing brain and result in long-term cognitive deficits when used for longer than 3 hours. The clinical significance of these findings is not clear. However, based on the available data, the window of vulnerability to these changes is believed to correlate with exposures in the third trimester of gestation through the first several months of life, but may extend out to approximately three years of age in humans (see PRECAUTIONS/Pregnancy, Pediatric Use, ANIMAL PHARMACOLOGY AND/OR TOXICOLOGY).

Some published studies in children suggest that similar deficits may occur after repeated or prolonged exposures to anesthetic agents early in life and may result in adverse cognitive or behavioral effects. These studies have substantial limitations, and it is not clear if the observed effects are due to the anesthetic/sedation drug administration or other factors such as the surgery or underlying illness.

Anesthetic and sedation drugs are a necessary part of the care of children needing surgery, other procedures, or tests that cannot be delayed, and no specific medications have been shown to be safer than any other. Decisions regarding the timing of any elective procedures requiring anesthesia should take into consideration the benefits of the procedure weighed against the potential risks.

PRECAUTIONS

Carcinogenesis, Mutagenesis, Impairment of Fertility:

Carcinogenesis

Long-term animal studies to evaluate the carcinogenic potential of etomidate have not been completed.

Mutagenesis

Studies to evaluate the mutagenic potential of etomidate have not been completed.

Impairment of Fertility

In a fertility and early embryonic development study in which male and female rats were treated intravenously with 0.31, 1.25, and 5 mg/kg/day etomidate (0.17, 0.68, and 2.7 times the human induction dose of 0.3 mg/kg based on body surface area) prior to mating, no adverse effects on fertility were noted.

Pregnancy

Risk Summary

There are no adequate and well-controlled studies in pregnant women. In animal reproduction studies, fetal deaths and reduced pup survival were noted after intravenous administration of etomidate to pregnant rats at doses 0.17 times the human induction dose of 0.3 mg/kg. Reduced pup survival was noted after intravenous administration of etomidate to pregnant rabbits at 1.6 times the human induction dose. Published studies in pregnant primates demonstrate that the administration of anesthetic and sedation drugs that block NMDA receptors and/or potentiate GABA activity during the period of peak brain development increases neuronal apoptosis in the developing brain of the offspring when used for longer than 3 hours. There are no data on pregnancy exposures in primates corresponding to periods prior to the third trimester in humans (See Data)

The estimated background risk of major birth defects and miscarriage for the indicated population is unknown. All pregnancies have a background risk of birth defect, loss, or other adverse outcomes. In the U.S. general population, the estimated background risk of major birth defects and miscarriage in clinically recognized pregnancies is 2% to 4% and 15% to 20%, respectively.

Data

Animal Data

No malformations or adverse fetal effects were noted in a study in which pregnant rats were intravenously administered 0.31, 1.25, or 5 mg/kg/day etomidate (0.17, 0.68, or 2.7 times the human induction dose of 0.3 mg/kg based on body surface area) during organogenesis (Gestation Days 6–15).

Reduced pup survival was noted in all doses tested in a study in which pregnant rabbits were intravenously administered 1.5 or 4.5 mg/kg/day etomidate (1.6 or 4.9 times the human induction dose of 0.3 mg/kg based on body surface area) during organogenesis (Gestation Day 6–18). These doses also produced maternal toxicity (increased mortality).

Increased still born fetuses and decreased pup survival was noted at all doses tested in a study where pregnant rats were intravenously administered 0.31, 1.25, or 5 mg/kg/day etomidate (0.17, 0.68, or 2.7 times the human induction dose of 0.3 mg/kg based on body surface area) during gestation and throughout lactation (Gestation Day 16 through Lactation Day 21). These doses also produced maternal toxicity (decreased food consumption and increased mortality). In this study, offspring were not evaluated for sexual maturation, neurobehavioral function including learning and memory, or reproductive function.

In a published study in primates, administration of an anesthetic dose of ketamine for 24 hours on Gestation Day 122 increased neuronal apoptosis in the developing brain of the fetus. In other published studies, administration of either isoflurane or propofol for 5 hours on Gestation Day 120 resulted in increased neuronal and oligodendrocyte apoptosis in the developing brain of the offspring. With respect to brain development, this time period corresponds to the third trimester of gestation in the human. The clinical significance of these findings is not clear; however, studies in juvenile animals suggest neuroapoptosis correlates with long-term cognitive deficits (See WARNINGS/Pediatric Neurotoxicity, PRECAUTIONS/Pregnancy, ANIMAL TOXICOLOGY AND/OR PHARMACOLOGY).

Labor and Delivery

There are insufficient data to support use of intravenous AMIDATE in obstetrics, including Caesarean section deliveries. Therefore, such use is not recommended.

Nursing Mothers

It is not known whether this drug is excreted in human milk. Because many drugs are excreted in human milk, caution should be exercised when AMIDATE is administered to a nursing mother.

Pediatric Use

There are inadequate data for AMIDATE to make dosage recommendations for induction of anesthesia in patients below the age of ten (10) years; therefore, such use is not recommended (see also DOSAGE AND ADMINISTRATION).

Published juvenile animal studies demonstrate that the administration of anesthetic and sedation drugs, such as AMIDATE, that either block NMDA receptors or potentiate the activity of GABA during the period of rapid brain growth or synaptogenesis, results in widespread neuronal and oligodendrocyte cell loss in the developing brain and alterations in synaptic morphology and neurogenesis. Based on comparisons across species, the window of vulnerability to these changes is believed to correlate with exposures in the third trimester of gestation through the first several months of life, but may extend out to approximately 3 years of age in humans.

In primates, exposure to 3 hours of ketamine that produced a light surgical plane of anesthesia did not increase neuronal cell loss, however, treatment regimens of 5 hours or longer of isoflurane increased neuronal cell loss. Data from isoflurane-treated rodents and ketamine-treated primates suggest that the neuronal and oligodendrocyte cell losses are associated with prolonged cognitive deficits in learning and memory. The clinical significance of these nonclinical findings is not known, and healthcare providers should balance the benefits of appropriate anesthesia in pregnant women, neonates, and young children who require procedures with the potential risks suggested by the nonclinical data. (See WARNINGS/Pediatric Neurotoxicity, PRECAUTIONS/Pregnancy, and ANIMAL PHARMACOLOGY AND/OR TOXICOLOGY)

Geriatric Use

Clinical data indicates that AMIDATE may induce cardiac depression in elderly patients, particularly those with hypertension (see CLINICAL PHARMACOLOGY and OTHER ADVERSE OBSERVATIONS, Circulatory System).

Elderly patients may require lower doses of AMIDATE than younger patients. Age-related differences in pharmacokinetic parameters have been observed in clinical studies (see CLINICAL PHARMACOLOGY and DOSAGE AND ADMINISTRATION).

This drug is known to be substantially excreted by the kidney, and the risk of toxic reactions to this drug may be greater in patients with impaired renal function. Because elderly patients are more likely to have decreased renal function, care should be taken in dose selection and it may be useful to monitor renal function.

Plasma Cortisol Levels

Induction doses of etomidate have been associated with reduction in plasma cortisol and aldosterone concentrations (see CLINICAL PHARMACOLOGY). These have not been associated with changes in vital signs or evidence of increased mortality; however, where concern exists for patients undergoing severe stress, exogenous replacement should be considered.

Information for Patients

Effect of anesthetic and sedation drugs on early brain development

Studies conducted in young animals and children suggest repeated or prolonged use of general anesthetic or sedation drugs in children younger than 3 years may have negative effects on their developing brains. Discuss with parents and caregivers the benefits, risks, and timing and duration of surgery or procedures requiring anesthetic and sedation drugs (See WARNINGS/Pediatric Neurotoxicity).

ADVERSE REACTIONS

The most frequent adverse reactions associated with use of intravenous AMIDATE are transient venous pain on injection and transient skeletal muscle movements, including myoclonus:

1. Transient venous pain was observed immediately following intravenous injection of etomidate in about 20% of the patients, with considerable difference in the reported incidence (1.2% to 42%). This pain is usually described as mild to moderate in severity but it is occasionally judged disturbing. The observation of venous pain is not associated with a more than usual incidence of thrombosis or thrombophlebitis at the injection site. Pain also appears to be less frequently noted when larger, more proximal arm veins are employed and it appears to be more frequently noted when smaller, more distal, hand or wrist veins are employed.

2. Transient skeletal muscle movements were noted following use of intravenous etomidate in about 32% of the patients, with considerable difference in the reported incidence (22.7% to 63%). Most of these observations were judged mild to moderate in severity but some were judged disturbing. The incidence of disturbing movements was less when 0.1 mg of fentanyl was given immediately before induction. These movements have been classified as myoclonic in the majority of cases (74%), but averting movements (7%), tonic movements (10%), and eye movements (9%) have also been reported. No exact classification is available, but these movements may also be placed into three groups by location:

a. Most movements are bilateral. The arms, legs, shoulders, neck, chest wall, trunk and all four extremities have been described in some cases, with one or more of these muscle groups predominating in each individual case. Results of electroencephalographic studies suggest that these muscle movements are a manifestation of disinhibition of cortical activity; cortical electroencephalograms, taken during periods when these muscle movements were observed, have failed to reveal seizure activity.

b. Other movements are described as either unilateral or having a predominance of activity of one side over the other. These movements sometimes resemble a localized response to some stimuli, such as venous pain on injection, in the lightly anesthetized patient (averting movements). Any muscle group or groups may be involved, but a predominance of movement of the arm in which the intravenous infusion is started is frequently noted.

c. Still other movements probably represent a mixture of the first two types.

Skeletal muscle movements appear to be more frequent in patients who also manifest venous pain on injection.

Other Adverse Observations

Respiratory System: Hyperventilation, hypoventilation, apnea of short duration (5 to 90 seconds with spontaneous recovery); laryngospasm, hiccup and snoring suggestive of partial upper airway obstruction have been observed in some patients. These conditions were managed by conventional countermeasures.

Circulatory System: Hypertension, hypotension, tachycardia, bradycardia and other arrhythmias have occasionally been observed during induction and maintenance of anesthesia. One case of severe hypotension and tachycardia, judged to be anaphylactoid in character, has been reported.

Geriatric patients, particularly those with hypertension, may be at increased risk for the development of cardiac depression following etomidate administration (see CLINICAL PHARMACOLOGY).

Gastrointestinal System: Postoperative nausea and/or vomiting following induction of anesthesia with etomidate is probably no more frequent than the general incidence. When etomidate was used for both induction and maintenance of anesthesia in short procedures such as dilation and curettage, or when insufficient analgesia was provided, the incidence of postoperative nausea and/or vomiting was higher than that noted in control patients who received thiopental.

OVERDOSAGE

Overdosage may occur from too rapid or repeated injections. Too rapid injection may be followed by a fall in blood pressure. No adverse cardiovascular or respiratory effects attributable to AMIDATE overdose have been reported.

In the event of suspected or apparent overdosage, the drug should be discontinued, a patent airway established (intubate, if necessary) or maintained and oxygen administered with assisted ventilation, if necessary.

DOSAGE AND ADMINISTRATION

Do not administer unless solution is clear and container is undamaged. Discard unused portion (see DOSAGE AND ADMINISTRATION).

AMIDATE is intended for administration only by the intravenous route (see CLINICAL PHARMACOLOGY). The dose for induction of anesthesia in adult patients and in pediatric patients above the age of ten (10) years will vary between 0.2 mg/kg and 0.6 mg/kg of body weight, and it must be individualized in each case. The usual dose for induction in these patients is 0.3 mg/kg, injected over a period of 30 to 60 seconds. There are inadequate data to make dosage recommendations for induction of anesthesia in patients below the age of ten (10) years; therefore, such use is not recommended. Geriatric patients may require reduced doses of etomidate.

Smaller increments of intravenous AMIDATE may be administered to adult patients during short operative procedures to supplement subpotent anesthetic agents, such as nitrous oxide. The dosage employed under these circumstances, although usually smaller than the original induction dose, must be individualized. There are insufficient data to support this use of etomidate for longer adult procedures or for any procedures in pediatric patients; therefore, such use is not recommended. The use of intravenous fentanyl and other neuroactive drugs employed during the conduct of anesthesia may alter the etomidate dosage requirements. Consult the prescribing information for all other such drugs before using.

Premedication: AMIDATE is compatible with commonly administered pre-anesthetic medications, which may be employed as indicated. See also CLINICAL PHARMACOLOGY, ADVERSE REACTIONS, and dosage recommendations for maintenance of anesthesia.

AMIDATE anesthesia does not significantly alter the usual dosage requirements of neuromuscular blocking agents employed for endotracheal intubation or other purposes shortly after induction of anesthesia.

Parenteral drug products should be inspected visually for particulate matter and discoloration prior to administration, whenever solution and container permit.

To prevent needle-stick injuries, needles should not be recapped, purposely bent, or broken by hand.

HOW SUPPLIED

AMIDATE (Etomidate Injection, USP) is supplied in single-dose containers as follows:

Store at 20 °to 25° (68 to 77°F). [See USP Controlled Room Temperature]

Product repackaged by: Henry Schein, Inc., Bastian, VA 24314
From Original Manufacturer/Distributor's NDC and Unit of Sale | To Henry Schein Repackaged Product NDC and Unit of Sale | Total Strength/Total Volume (Concentration) per unit
NDC 0409-6695-01 Tray of 10 Single-dose Fliptop Vials | NDC 0404-9811-10 1 10 mL Single Dose Fliptop Vial in a bag (Vial bears NDC 0409-6695-11) | 20 mg/10 mL (2 mg/mL)

ANIMAL TOXICOLOGY AND/OR PHARMACOLOGY

Published studies in animals demonstrate that the use of anesthetic agents during the period of rapid brain growth or synaptogenesis results in widespread neuronal and oligodendrocyte cell loss in the developing brain and alterations in synaptic morphology and neurogenesis. Based on comparisons across species, the window of vulnerability to these changes is believed to correlate with exposures in the third trimester through the first several months of life, but may extend out to approximately 3 years of age in humans.

In primates, exposure to 3 hours of an anesthetic regimen that produced a light surgical plane of anesthesia did not increase neuronal cell loss, however, treatment regimens of 5 hours or longer increased neuronal cell loss. Data in rodents and in primates suggest that the neuronal and oligodendrocyte cell losses are associated with subtle but prolonged cognitive deficits in learning and memory. The clinical significance of these nonclinical findings is not known, and healthcare providers should balance the benefits of appropriate anesthesia in neonates and young children who require procedures against the potential risks suggested by the nonclinical data (See WARNINGS/Pediatric Neurotoxicity, PRECAUTIONS/Pregnancy, Pediatric Use).

Distributed by Hospira, Inc., Lake Forest, IL 60045 USA

LAB-0922-6.0

Revised: 04/2022